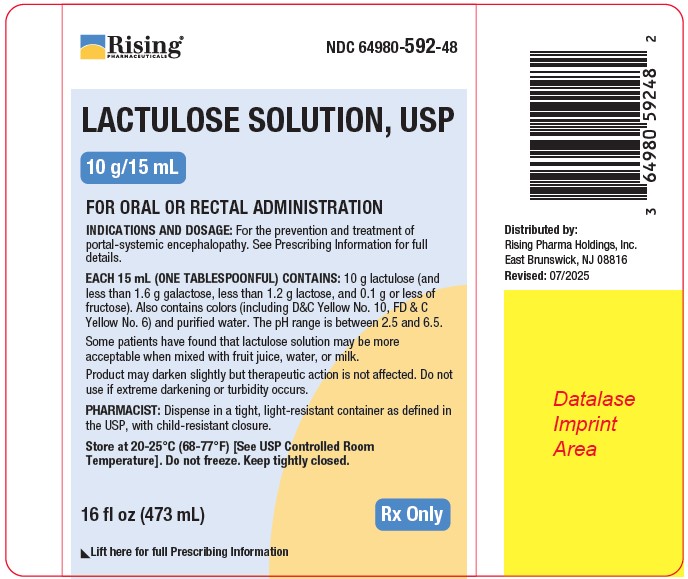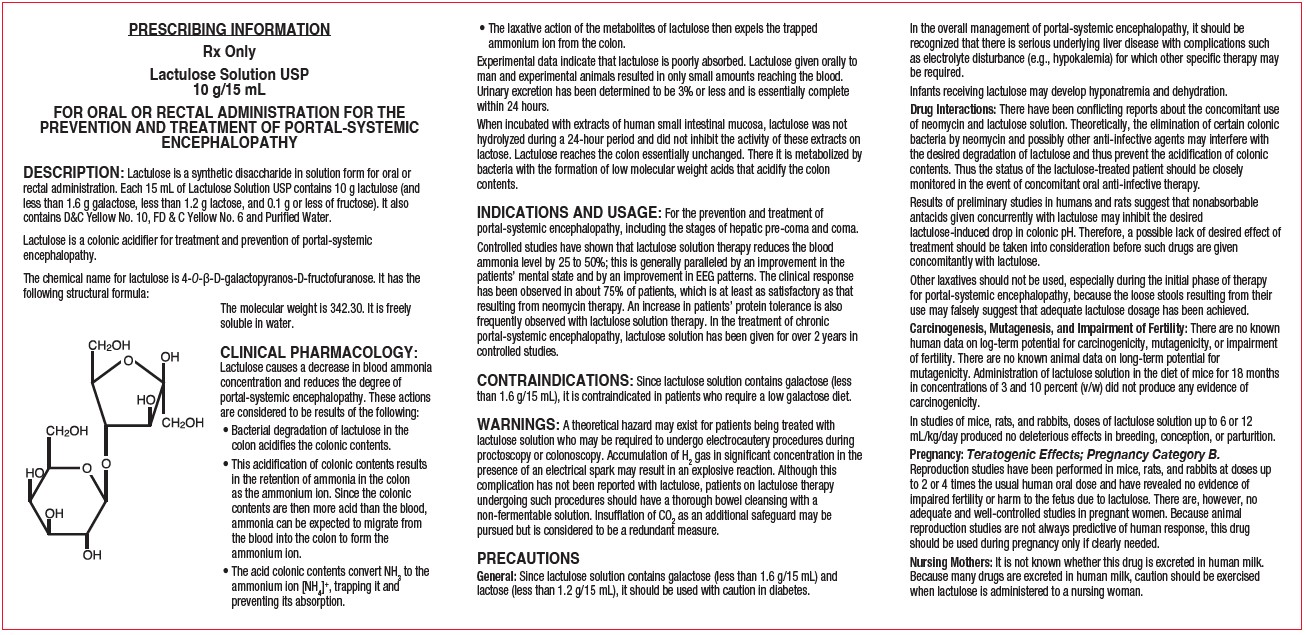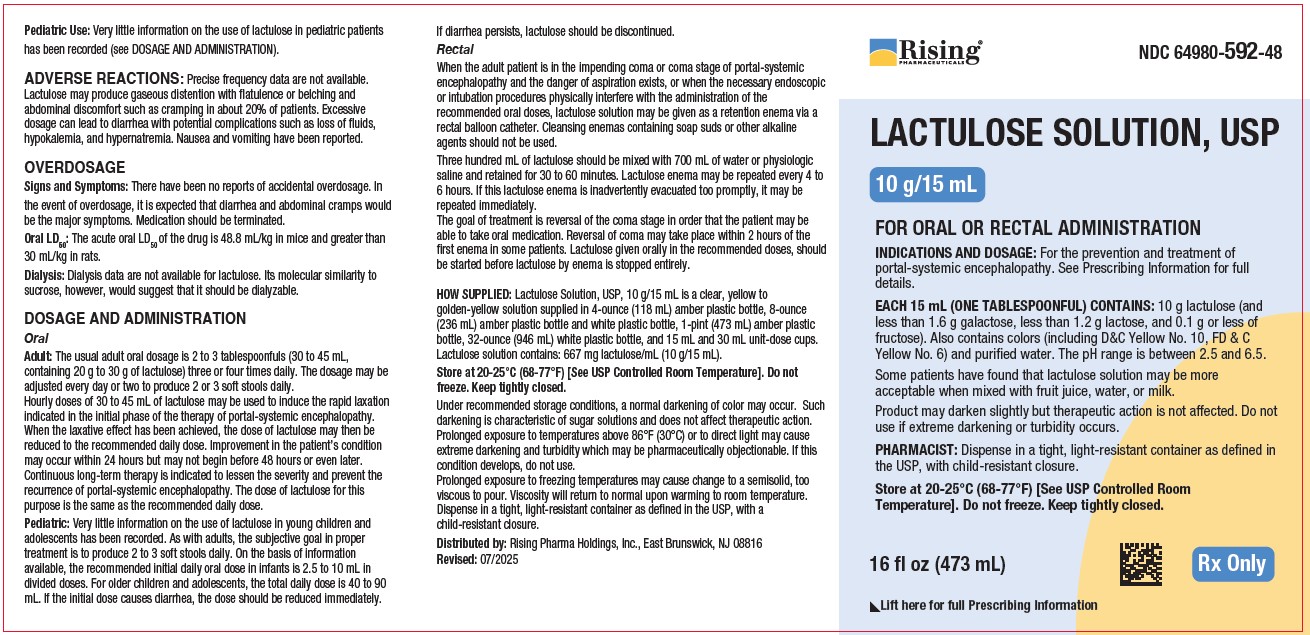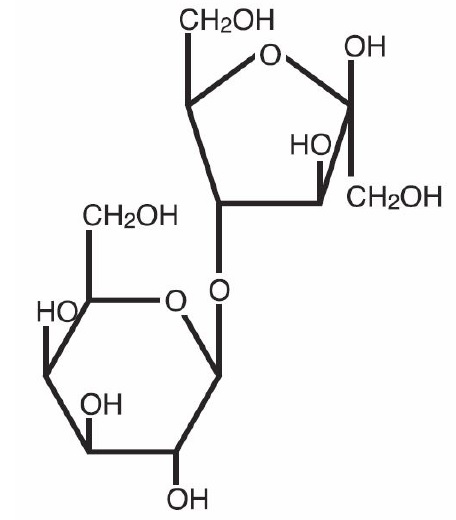 DRUG LABEL: Lactulose Solution
NDC: 64980-592 | Form: SOLUTION
Manufacturer: Rising Pharma Holdings, Inc.
Category: prescription | Type: HUMAN PRESCRIPTION DRUG LABEL
Date: 20260112

ACTIVE INGREDIENTS: LACTULOSE 10 g/15 mL
INACTIVE INGREDIENTS: FD&C YELLOW NO. 6; D&C YELLOW NO. 10; WATER

Lactulose Solution USP, 10 g/15 mL
Rising Pharma Holdings, Inc.

DESCRIPTION

Lactulose is a synthetic disaccharide in solution form for oral or rectal administration. Each 15 mL of Lactulose Solution USP contains 10 g lactulose (and less than 1.6 g galactose, less than 1.2 g lactose, and 0.1 g or less of fructose). It also contains D&C Yellow No. 10, FD & C Yellow No. 6 and Purified Water.
Lactulose is a colonic acidifier for treatment and prevention of portal-systemic encephalopathy.
The chemical name for lactulose is 4-0-ß-D-galactopyranos-D-fructofuranose. It has the following structural formula:

The molecular weight is 342.30. It is freely soluble in water.

CLINICAL PHARMACOLOGY

Lactulose causes a decrease in blood ammonia concentration and reduces the degree of portal-systemic encephalopathy. These actions are considered to be results of the following:

- Bacterial degradation of lactulose in the colon acidifies the colonic contents.
- This acidification of colonic contents results in the retention of ammonia in the colon as the ammonium ion. Since the colonic contents are then more acid than the blood, ammonia can be expected to migrate from the blood into the colon to form the ammonium ion.
- The acid colonic contents convert NH 3 to the ammonium ion [NH 4] ^+, trapping it and preventing its absorption.
- The laxative action of the metabolites of lactulose then expels the trapped ammonium ion from the colon.

Experimental data indicate that lactulose is poorly absorbed. Lactulose given orally to man and experimental animals resulted in only small amounts reaching the blood. Urinary excretion has been determined to be 3% or less and is essentially complete within 24 hours.
When incubated with extracts of human small intestinal mucosa, lactulose was not hydrolyzed during a 24-hour period and did not inhibit the activity of these extracts on lactose. Lactulose reaches the colon essentially unchanged. There it is metabolized by bacteria with the formation of low molecular weight acids that acidify the colon contents.

INDICATIONS AND USAGE

For the prevention and treatment of portal-systemic encephalopathy, including the stages of hepatic pre-coma and coma.
Controlled studies have shown that lactulose solution therapy reduces the blood ammonia level by 25 to 50%; this is generally paralleled by an improvement in the patients’ mental state and by an improvement in EEG patterns. The clinical response has been observed in about 75% of patients, which is at least as satisfactory as that resulting from neomycin therapy. An increase in patients’ protein tolerance is also frequently observed with lactulose solution therapy. In the treatment of chronic portal-systemic encephalopathy, lactulose solution has been given for over 2 years in controlled studies.

CONTRAINDICATIONS

Since lactulose solution contains galactose (less than 1.6 g/15 mL), it is contraindicated in patients who require a low galactose diet.

WARNINGS

A theoretical hazard may exist for patients being treated with lactulose solution who may be required to undergo electrocautery procedures during proctoscopy or colonoscopy. Accumulation of H2 gas in significant concentration in the presence of an electrical spark may result in an explosive reaction. Although this complication has not been reported with lactulose, patients on lactulose therapy undergoing such procedures should have a thorough bowel cleansing with a non-fermentable solution. Insufflation of CO2 as an additional safeguard may be pursued but is considered to be a redundant measure.

PRECAUTIONS

General: Since lactulose solution contains galactose (less than 1.6 g/15 mL) and lactose (less than 1.2 g/15 mL), it should be used with caution in diabetes.

In the overall management of portal-systemic encephalopathy, it should be recognized that there is serious underlying liver disease with complications such as electrolyte disturbance (e.g., hypokalemia) for which other specific therapy may be required.

Infants receiving lactulose may develop hyponatremia and dehydration.

Drug Interactions

There have been conflicting reports about the concomitant use of neomycin and lactulose solution. Theoretically, the elimination of certain colonic bacteria by neomycin and possibly other anti-infective agents may interfere with the desired degradation of lactulose and thus prevent the acidification of colonic contents. Thus the status of the lactulose-treated patient should be closely monitored in the event of concomitant oral anti-infective therapy.
Results of preliminary studies in humans and rats suggest that nonabsorbable antacids given concurrently with lactulose may inhibit the desired lactulose-induced drop in colonic pH. Therefore, a possible lack of desired effect of treatment should be taken into consideration before such drugs are given concomitantly with lactulose.
Other laxatives should not be used, especially during the initial phase of therapy for portal-systemic encephalopathy, because the loose stools resulting from their use may falsely suggest that adequate lactulose dosage has been achieved.

Carcinogenesis, Mutagenesis, and Impairment of Fertility

There are no known human data on log-term potential for carcinogenicity, mutagenicity, or impairment of fertility. There are no known animal data on long-term potential for mutagenicity. Administration of lactulose solution in the diet of mice for 18 months in concentrations of 3 and 10 percent (v/w) did not produce any evidence of carcinogenicity.
In studies of mice, rats, and rabbits, doses of lactulose solution up to 6 or 12 mL/kg/day produced no deleterious effects in breeding, conception, or parturition.

Pregnancy: Teratogenic Effects; Pregnancy Category B.

Reproduction studies have been performed in mice, rats, and rabbits at doses up to 2 or 4 times the usual human oral dose and have revealed no evidence of impaired fertility or harm to the fetus due to lactulose. There are, however, no adequate and well-controlled studies in pregnant women. Because animal reproduction studies are not always predictive of human response, this drug should be used during pregnancy only if clearly needed.

Nursing Mothers

It is not known whether this drug is excreted in human milk. Because many drugs are excreted in human milk, caution should be exercised when lactulose is administered to a nursing woman.

Pediatric Use

Very little information on the use of lactulose in pediatric patients has been recorded (see DOSAGE AND ADMINISTRATION).

ADVERSE REACTIONS

Precise frequency data are not available. Lactulose may produce gaseous distention with flatulence or belching and abdominal discomfort such as cramping in about 20% of patients. Excessive dosage can lead to diarrhea with potential complications such as loss of fluids, hypokalemia, and hypernatremia. Nausea and vomiting have been reported.

OVERDOSAGE

Signs and Symptoms: There have been no reports of accidental overdosage. In the event of overdosage, it is expected that diarrhea and abdominal cramps would be the major symptoms. Medication should be terminated.

Oral LD50: The acute oral LD50 of the drug is 48.8 mL/kg in mice and greater than 30 mL/kg in rats.

Dialysis: Dialysis data are not available for lactulose. Its molecular similarity to sucrose, however, would suggest that it should be dialyzable.

DOSAGE AND ADMINISTRATION

Oral
Adult: The usual adult oral dosage is 2 to 3 tablespoonfuls (30 to 45 mL, containing 20 g to 30 g of lactulose) three or four times daily. The dosage may be adjusted every day or two to produce 2 or 3 soft stools daily.

Hourly doses of 30 to 45 mL of lactulose may be used to induce the rapid laxation indicated in the initial phase of the therapy of portal-systemic encephalopathy. When the laxative effect has been achieved, the dose of lactulose may then be reduced to the recommended daily dose. Improvement in the patient’s condition may occur within 24 hours but may not begin before 48 hours or even later.
Continuous long-term therapy is indicated to lessen the severity and prevent the recurrence of portal-systemic encephalopathy. The dose of lactulose for this purpose is the same as the recommended daily dose.

Pediatric: Very little information on the use of lactulose in young children and adolescents has been recorded. As with adults, the subjective goal in proper treatment is to produce 2 to 3 soft stools daily. On the basis of information available, the recommended initial daily oral dose in infants is 2.5 to 10 mL in divided doses. For older children and adolescents, the total daily dose is 40 to 90 mL. If the initial dose causes diarrhea, the dose should be reduced immediately. If diarrhea persists, lactulose should be discontinued.

Rectal
When the adult patient is in the impending coma or coma stage of portal-systemic encephalopathy and the danger of aspiration exists, or when the necessary endoscopic or intubation procedures physically interfere with the administration of the recommended oral doses, lactulose solution may be given as a retention enema via a rectal balloon catheter. Cleansing enemas containing soap suds or other alkaline agents should not be used.
Three hundred mL of lactulose should be mixed with 700 mL of water or physiologic saline and retained for 30 to 60 minutes. Lactulose enema may be repeated every 4 to 6 hours. If this lactulose enema is inadvertently evacuated too promptly, it may be repeated immediately.
The goal of treatment is reversal of the coma stage in order that the patient may be able to take oral medication. Reversal of coma may take place within 2 hours of the first enema in some patients. Lactulose given orally in the recommended doses, should be started before lactulose by enema is stopped entirely.

HOW SUPPLIED

Lactulose Solution, USP, 10 g/15 mL is a clear, yellow to golden-yellow solution supplied in 4-ounce (118 mL) amber plastic bottle, 8-ounce (236 mL) white plastic bottle, 1-pint (473 mL) amber plastic bottle, 32-ounce (946 mL) white plastic bottle, and 15 mL and 30 mL unit-dose cups.
Lactulose solution contains: 667 mg lactulose/mL (10 g/15 mL).
Store at 20-25°C (68-77°F) [See USP Controlled Room Temperature]. Do not freeze. Keep tightly closed.
Under recommended storage conditions, a normal darkening of color may occur. Such darkening is characteristic of sugar solutions and does not affect therapeutic action.

Prolonged exposure to temperatures above 86°F (30°C) or to direct light may cause extreme darkening and turbidity which may be pharmaceutically objectionable. If this condition develops, do not use.
Prolonged exposure to freezing temperatures may cause change to a semisolid, too viscous to pour. Viscosity will return to normal upon warming to room temperature.

Dispense in a tight, light-resistant container as defined in the USP, with a child-resistant closure.

Distributed by:

Rising Pharma Holdings, Inc.

East Brunswick, NJ 08816

Revised: 08/2025

PACKAGE LABEL

LACTULOSE SOLUTION, USP 10 g/15 mL

FOR ORAL OR RECTAL ADMINISTRATION

INDICATION AND DOSAGE: For the prevention and treatment of portal-systemic encephalopathy. See Prescribing Information for full details.

EACH 15 mL (ONE TABLESPOONFUL) CONTAINS: 10 g lactulose (and less than 1.6 g galactose, less than 1.2 g lactose, and 0.1 g or less of fructose). Also contains colors (including D&C Yellow No. 10, FD & C Yellow No. 6) and purified water. The pH range is between 2.5 and 6.5. Some patients have found that lactulose solution may be more acceptable when mixed with fruit juice, water, or milk.

Product may darken slightly but therapeutic action is not affected. Do not use if extreme darkening or turbidity occurs.

PHARMACIST: Dispense in a tight, light-resistant container as defined in the USP, with child-resistant closure.

Store at 20-25°C (68-77°F) [See USP Controlled Room Temperature]. Do not freeze. Keep tightly closed.

Distributed by:

Rising Pharma Holdings, Inc.

East Brunswick, NJ 08816

Revised: 08/2025

NDC 64980-592-48

16 fl oz (473 mL)

Rx Only